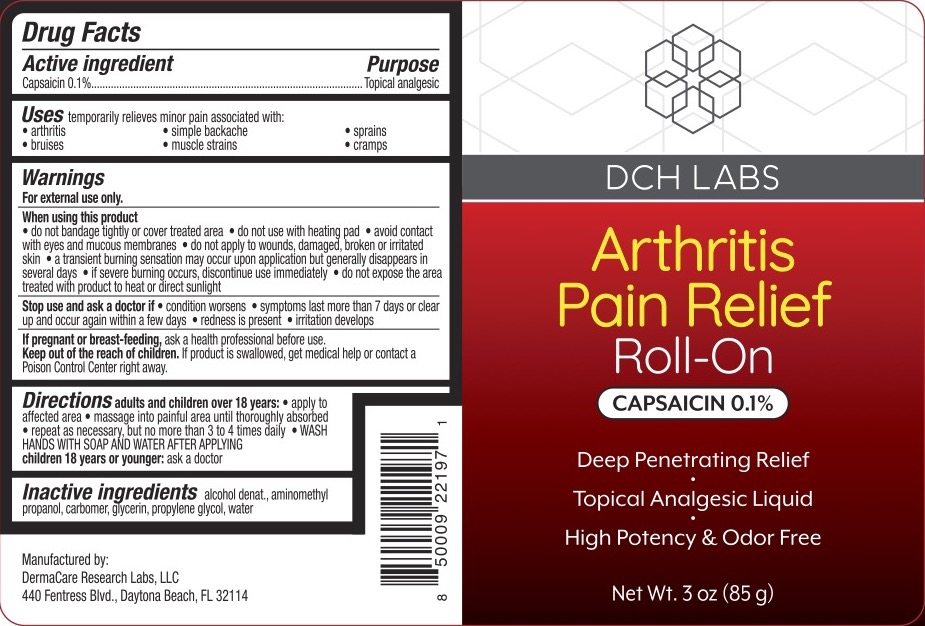 DRUG LABEL: DCH Arthritis Pain Relief Roll-On
NDC: 72839-026 | Form: GEL
Manufacturer: Derma Care Research Labs, LLC
Category: otc | Type: HUMAN OTC DRUG LABEL
Date: 20241219

ACTIVE INGREDIENTS: CAPSAICIN 0.1 g/100 g
INACTIVE INGREDIENTS: CARBOMER 940; WATER; GLYCERIN; ALCOHOL; AMINOMETHYLPROPANOL; PROPYLENE GLYCOL

DCH Arthritis Pain Relief Roll-on 0.1%

ACTIVE INGREDIENT

Capsaicin 0.1%

PURPOSE

Topical Analgesic

INDICATIONS AND USAGE

Temporarily relieves minor pain associated with arthritis, simple backache, sprains, bruises, muscle strains, and cramps.

WARNINGS

For external use only.

When using this product do not bandage tightly or cover treated area, do not use with heating pad, avoid contact with eyes and mucous membranes, do not apply to wounds, damaged, broken or irritated skin, a transient burning sensation may occur upon application but generally disappears in several days, if severe burning occurs, discontinue use immediately, do not expose the area treated with product to heat or direct sunlight.

Stop use and ask a doctor if condition worsens, symptoms last more than 7 days or clear up and occur again within a few days, redness is present, or irritation develops.

PREGNANCY OR BREAST FEEDING

Ask a health professional before use.

KEEP OUT OF REACH OF CHILDREN

If product is swallowed, get medical help or contact a Poison Control Center right away.

DOSAGE AND ADMINISTRATION

Adults and children of 18 years: apply to affected area, massage into painful area until thoroughly absorbed, repeat as necessary, but no more than 3 to 4 times daily. WASH HANDS WITH SOAP AND WATER AFTER APPLYING. Children 18 years or younger: ask a doctor.

INACTIVE INGREDIENT

Alcohol denat., aminomethyl propanol, carbomer, glycerin, propylene glycol, water.